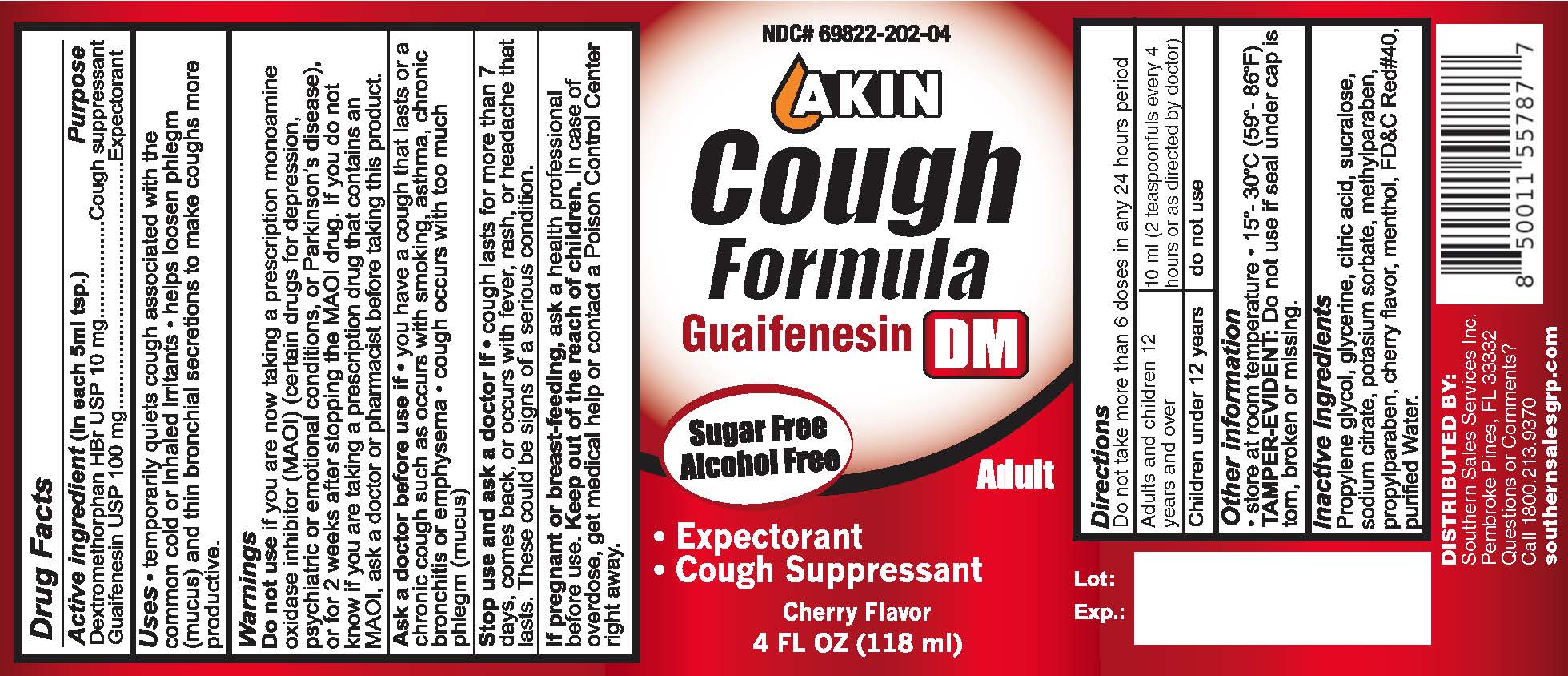 DRUG LABEL: Akin Cough Formula DM
NDC: 69822-202 | Form: LIQUID
Manufacturer: Southern Sales & Service, Inc.
Category: otc | Type: HUMAN OTC DRUG LABEL
Date: 20231129

ACTIVE INGREDIENTS: DEXTROMETHORPHAN HYDROBROMIDE 10 mg/5 mL; GUAIFENESIN 100 mg/5 mL
INACTIVE INGREDIENTS: PROPYLENE GLYCOL; GLYCERIN; CITRIC ACID MONOHYDRATE; SUCRALOSE; SODIUM CITRATE; POTASSIUM SORBATE; METHYLPARABEN; PROPYLPARABEN; CHERRY; MENTHOL; FD&C RED NO. 40; WATER

Akin Cough Formula DM

(in each 5ml tsp.) Active ingredient

Dextromethorphan HBr USP 10 mg Guaifenesin USP 100 mg

Purpose

Cough suppressant

Expectorant

Uses

temporarily quiets cough associated with the common cold or inhaled irritants

helps loosen phlegm (mucus) and thin bronchial secretions to make coughs more productive.

Warnings

Do not use

if you are now taking a prescription monoamine oxidase inhibitor (MAOI) (certain drugs for depression, psychiatric or emotional conditions, or Parkinson’s disease), or for 2 weeks after stopping the MAOI drug. If you do not know if you are taking a prescription drug that contains an MAOI, ask a doctor or pharmacist before taking this product.

Ask a doctor before use if

- you have a cough that lasts or a chronic cough such as occurs with smoking, asthma, chronic bronchitis or emphysema
- cough occurs with too much phlegm (mucus)

Stop use and ask a doctor if

Cough lasts for more than 7 days, comes back, or occurs with fever, rash, or headache that lasts. These could be signs of a serious condition.

If pregnant or breast-feeding,

ask a health professional before use.

Keep out of the reach of children.

In case of overdose, get medical help or contact a Poison Control Center right away.

Directions

Do not take more than 6 doses in any 24 hour period

adults and children 12 years and over | 10 ml (2 teaspoonfuls every 4 hours or as directed by doctor)
Children under 12 years | do not use

Other information

- store at room temperature
- 15°- 30°C (59°- 86°F)
- TAMPER-EVIDENT: Do not use if seal under cap is torn, broken or missing.

Inactive ingredients

Propylene glycol, glycerine, citric acid, sucralose, sodium citrate, potassium sorbate, methylparaben, propylparaben, cherry flavor, menthol, FD&C Red#40, purified Water.